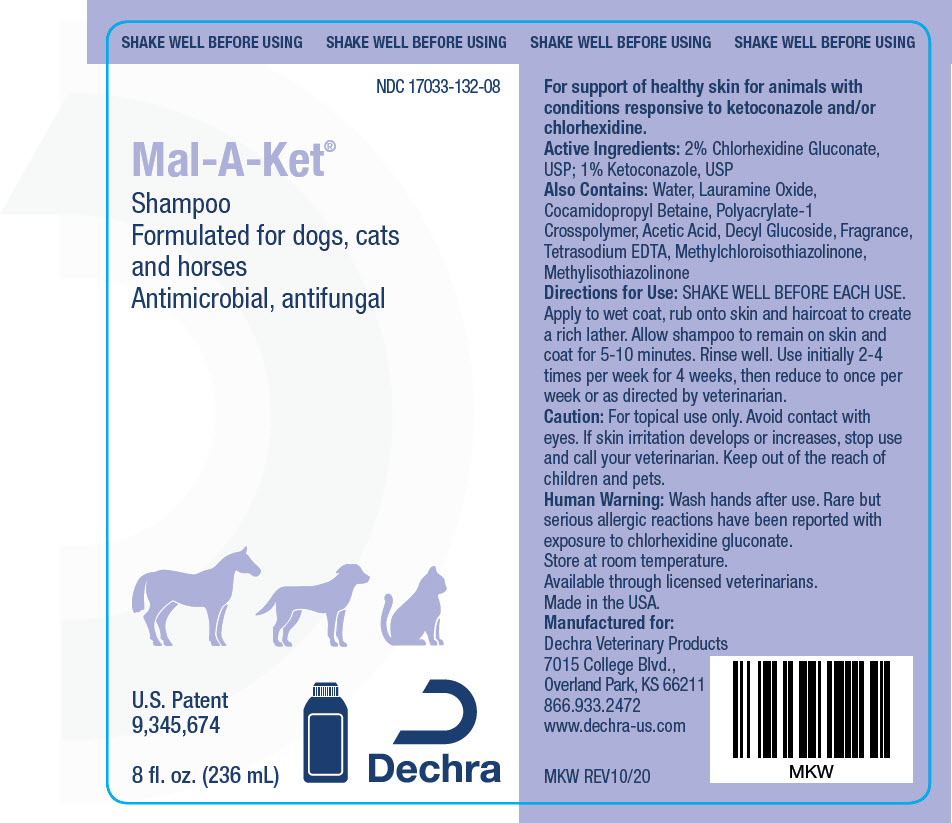 DRUG LABEL: Mal-A-Ket
NDC: 17033-132 | Form: SOLUTION
Manufacturer: Dechra Veterinary Products
Category: animal | Type: OTC ANIMAL DRUG LABEL
Date: 20210226

ACTIVE INGREDIENTS: CHLORHEXIDINE GLUCONATE 20 mg/1 mL; ACETIC ACID 20 mg/1 mL; KETOCONAZOLE 10 mg/1 mL
INACTIVE INGREDIENTS: LAURAMINE OXIDE; COCAMIDOPROPYL BETAINE; DECYL GLUCOSIDE; EDETATE SODIUM

Mal-A-Ket® Shampoo

VETERINARY INDICATIONS

For support of healthy skin for animals with conditions responsive to ketoconazole and/or chlorhexidine.

DESCRIPTION

Active Ingredients: 2% Chlorhexidine Gluconate, USP; 1% Ketoconazole, USP

Also Contains: Water, Lauramine Oxide, Cocamidopropyl Betaine, Polyacrylate-1 Crosspolymer, Acetic Acid, Decyl Glucoside, Fragrance, Tetrasodium EDTA, Methylchloroisothiazolinone, Methylisothiazolinone

DOSAGE AND ADMINISTRATION

Directions for Use: SHAKE WELL BEFORE EACH USE. Apply to wet coat, rub onto skin and haircoat to create a rich lather. Allow shampoo to remain on skin and coat for 5-10 minutes. Rinse well. Use initially 2-4 times per week for 4 weeks, then reduce to once per week or as directed by veterinarian.

SAFE HANDLING WARNING

Caution: For topical use only. Avoid contact with eyes. If skin irritation develops or increases, stop use and call your veterinarian. Keep out of the reach of children and pets.

WARNINGS

Human Warning: Wash hands after use. Rare but serious allergic reactions have been reported with exposure to chlorhexidine gluconate.

STORAGE AND HANDLING

Store at room temperature.

Available through licensed veterinarians.

Made in the USA.

Manufactured for:
Dechra Veterinary Products
7015 College Blvd.,
Overland Park, KS 66211
866.933.2472

MKW REV10/20

PRINCIPAL DISPLAY PANEL - 236 mL Bottle Label

SHAKE WELL BEFORE USING

NDC 17033-132-08

Mal-A-Ket®
Shampoo
Formulated for dogs, cats
and horses
Antimicrobial, antifungal

U.S. Patent
9,345,674

8 fl. oz. (236 mL)

Dechra